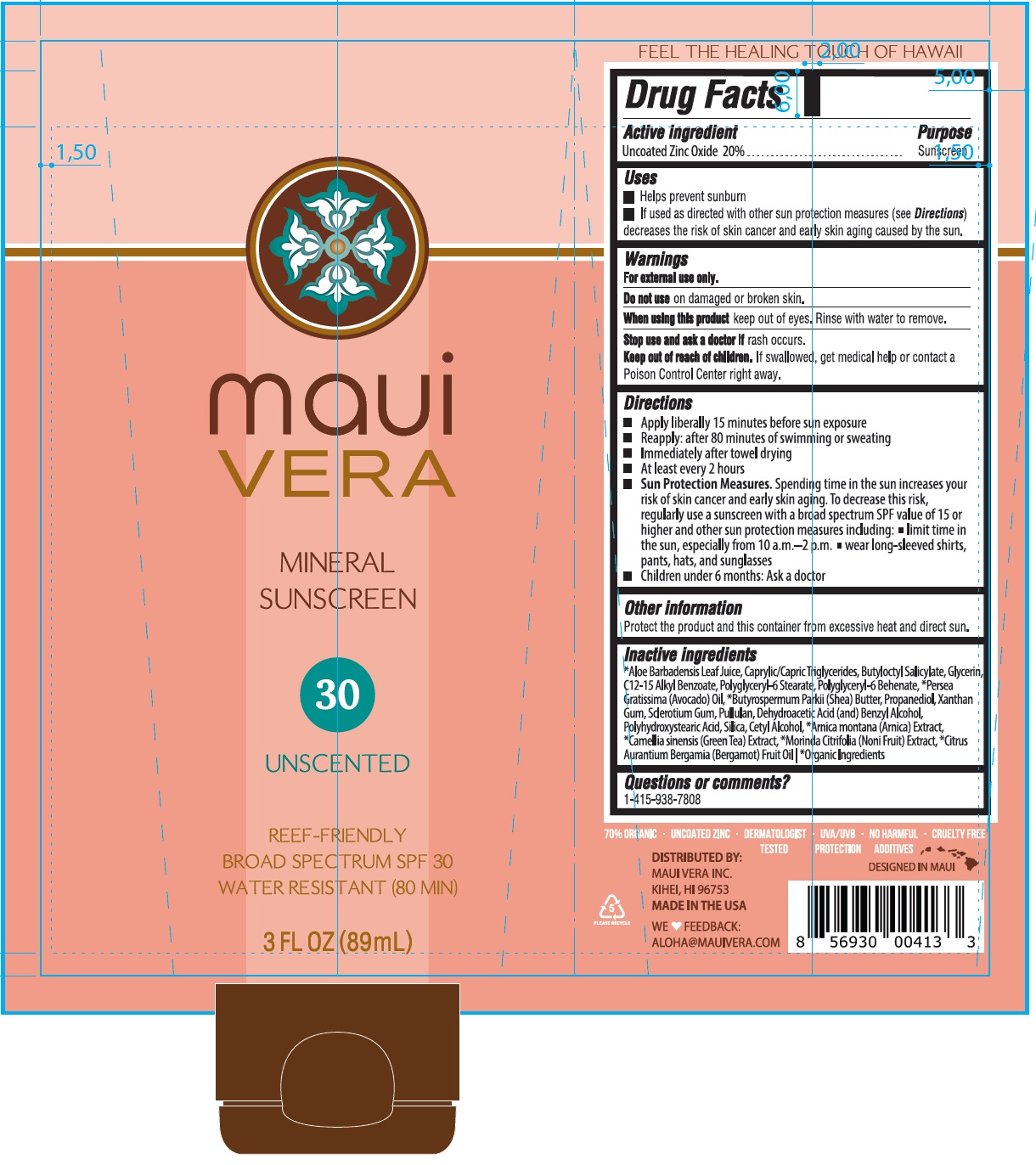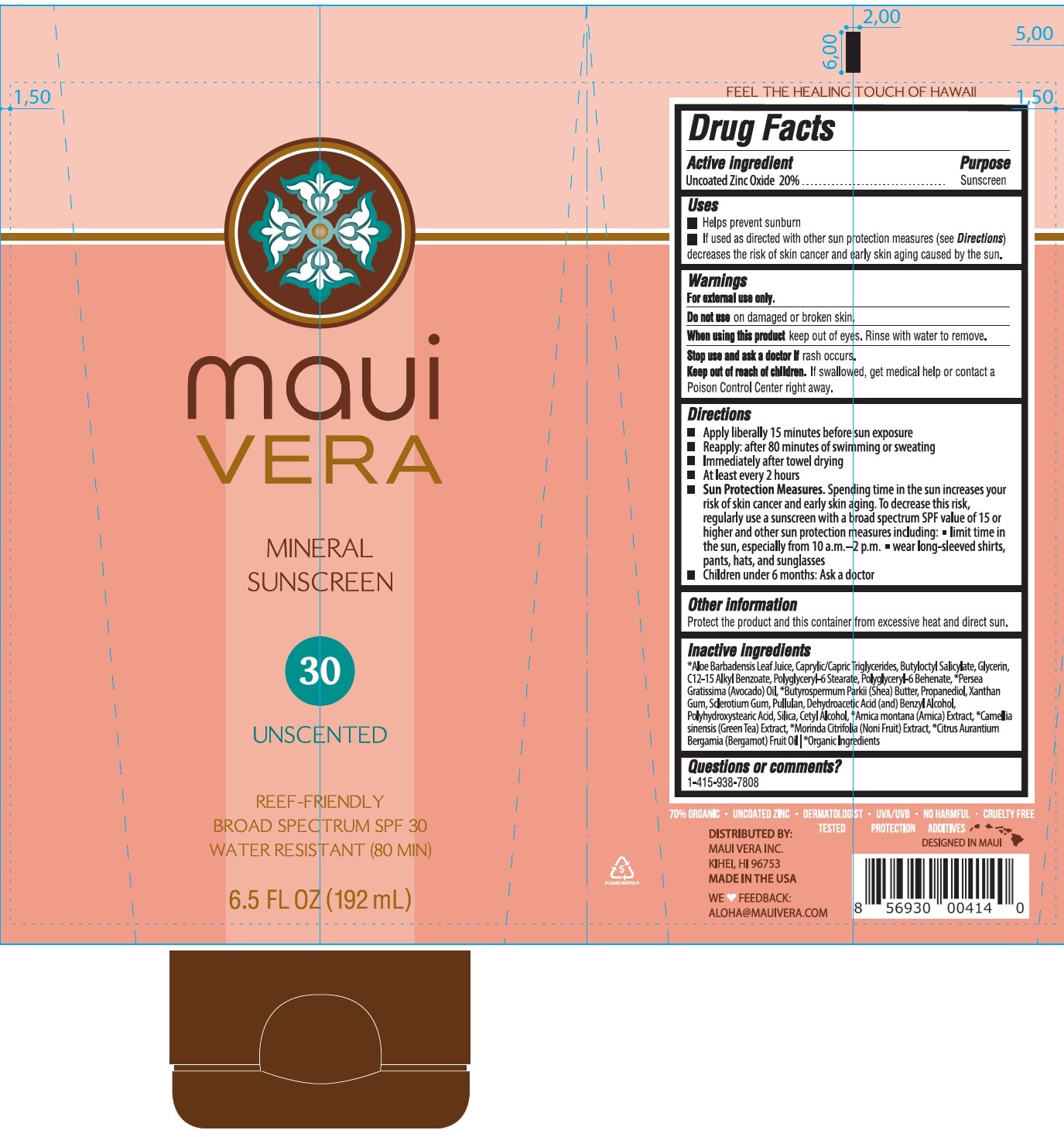 DRUG LABEL: Maui Vera Mineral Sunscreen SPF 30 Unscented
NDC: 81409-003 | Form: CREAM
Manufacturer: Maui Vera, Inc.
Category: otc | Type: HUMAN OTC DRUG LABEL
Date: 20241125

ACTIVE INGREDIENTS: ZINC OXIDE 200 mg/1 mL
INACTIVE INGREDIENTS: ALOE VERA LEAF; MEDIUM-CHAIN TRIGLYCERIDES; BUTYLOCTYL SALICYLATE; GLYCERIN; C12-15 ALKYL BENZOATE; POLYGLYCERYL-6 STEARATE; POLYGLYCERYL-6 BEHENATE; AVOCADO OIL; SHEA BUTTER; PROPANEDIOL; XANTHAN GUM; SCLEROTIUM GUM; PULLULAN; DEHYDROACETIC ACID; BENZYL ALCOHOL; SILICON DIOXIDE; CETYL ALCOHOL; ARNICA MONTANA WHOLE; GREEN TEA LEAF; NONI FRUIT; BERGAMOT OIL

Maui Vera Mineral Sunscreen SPF 30, Unscented

Active ingredient

Uncoated Zinc Oxide 20%

Purpose

Sunscreen

Uses

- Helps prevent sunburn
- If used as directed with other sun protection measures (see Directions) decreases the risk of skin cancer and early skin aging caused by the sun.

Warnings

For external use only.

Do not use

on damaged or broken skin.

When using this product

keep out of eyes. Rinse with water to remove.

Stop use and ask a doctor if

rash occurs.

Keep out of reach of children.

If swallowed, get medical help or contact a Poison Control Center right away.

Directions

- Apply liberally 15 minutes before sun exposure
- Reapply: after 80 minutes of swimming or sweating
- Immediately after towel drying
- At least every 2 hours
- Sun Protection Measures.Spending time in the sun increases your risk of skin cancer and early skin aging. To decrease this risk, regularly use a sunscreen with a broad spectrum SPF value of 15 or higher and other sun protection measures including:
- limit time in the sun, especially from 10 a.m. - 2 p.m.
- wear long-sleeved shirts, pants, hats, and sunglasses
- Children under 6 months: Ask a doctor

Other information

Protect the product and this container from excessive heat and direct sun.

Inactive ingredients

*Aloe Barbadensis Leaf Juice, Caprylic/Capric Triglycerides, Butyloctyl Salicylate, Glycerin, C12-15 Alkyl Benzoate, Polyglyceryl-6 Stearate, Polyglyceryl-6 Behenate, *Persea Gratissima (Avocado) Oil, Butyrospermum Parkii (Shea) Butter, Propanediol, Xanthan Gum, Sclerotium Gum, Pullulan, Dehydroacetic Acid (and) Benzyl Alcohol, Polyhydroxystearic Acid, Silica, Cetyl Alcohol, *Arnica montana (Arnica) Extract, *Camellia sinensis (Green Tea) Extract, *Morinda Citrifolia (Noni Fruit), *Citrus Aurantium Bergamia (Bergamot) Fruit Oil *Organic Ingredints

Questions or comments?

1-415-938-7808